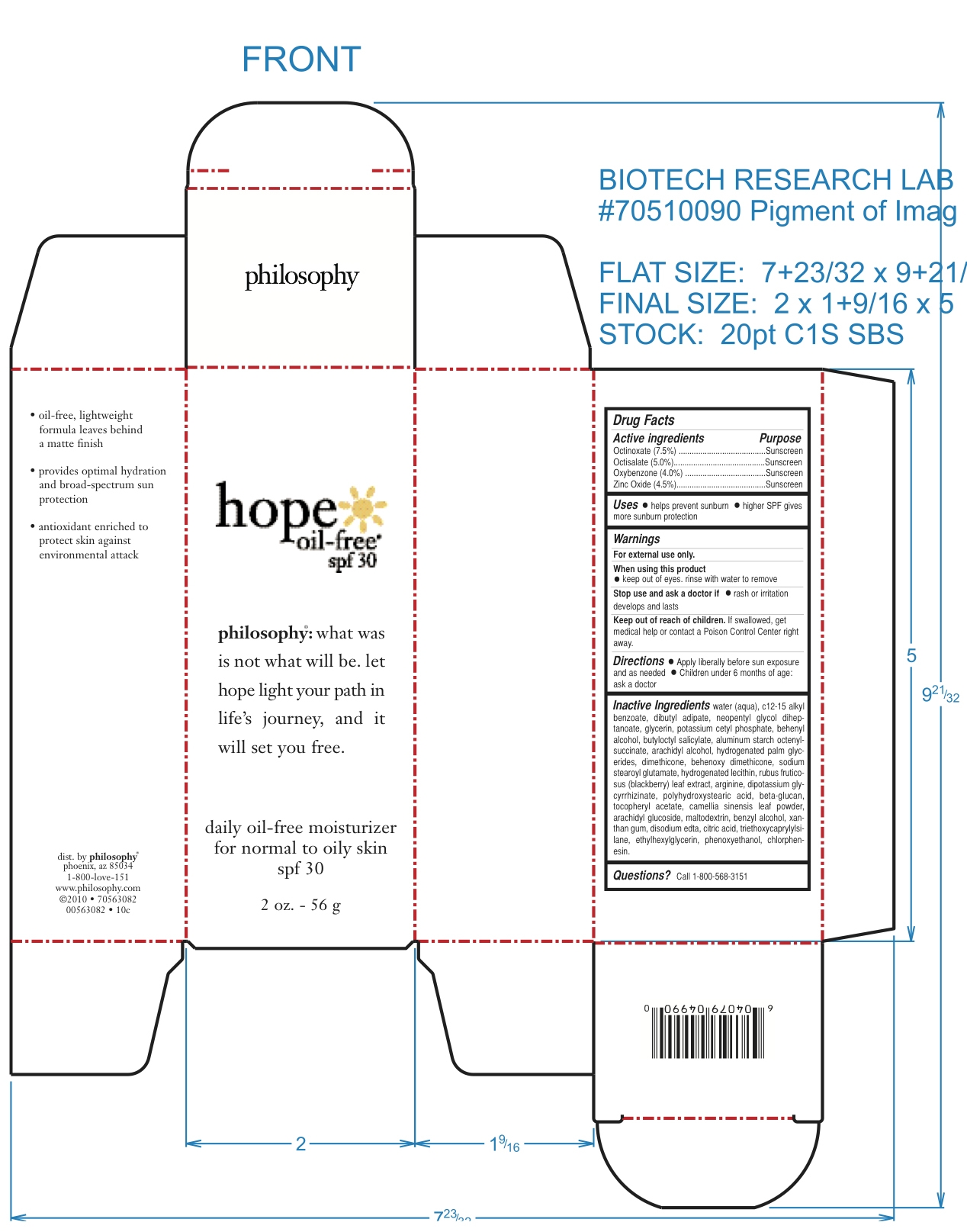 DRUG LABEL: Hope Oil Free Moisturizer SPF 30
NDC: 50184-6100 | Form: CREAM
Manufacturer: Philosophy, Inc.
Category: otc | Type: HUMAN OTC DRUG LABEL
Date: 20100405

ACTIVE INGREDIENTS: Octinoxate 75 mg/1 g; Octisalate 50 mg/1 g; Oxybenzone 40 mg/1 g; Zinc Oxide 45 mg/1 g
INACTIVE INGREDIENTS: WATER; ALKYL (C12-15) BENZOATE; NEOPENTYL GLYCOL DIHEPTANOATE; GLYCERIN; POTASSIUM CETYL PHOSPHATE; DOCOSANOL; BUTYLOCTYL SALICYLATE; ALUMINUM STARCH OCTENYLSUCCINATE; ARACHIDYL ALCOHOL; DIMETHICONE; MONOSODIUM GLUTAMATE ANHYDROUS; HYDROGENATED SOYBEAN LECITHIN; RUBUS FRUTICOSUS LEAF; ARGININE; .ALPHA.-TOCOPHEROL ACETATE, D-; GREEN TEA LEAF; MALTODEXTRIN; BENZYL ALCOHOL; XANTHAN GUM; EDETATE DISODIUM ; CITRIC ACID MONOHYDRATE; OCTYLTRIETHOXYSILANE; ETHYLHEXYLGLYCERIN; PHENOXYETHANOL; CHLORPHENESIN; GLYCYRRHIZINATE DIPOTASSIUM

Drug Facts

ACTIVE INGREDIENTS

OCTINOXATE (7.5%)

OCTISALATE (5.0%)

OXYBENZONE (4.0%)

ZINC OXIDE (4.5%)

INACTIVE INGREDIENTS:

WATER

C12-15 ALKYL BENZOATE

DIBUTYL ADIPATE

NEOPENTYL GLYCOL DIHEPTANOATE

GLYCERIN

POTASSIUM CETYL PHOSPHATE

BEHENYL ALCOHOL

BUTYLOCTYL SALICYLATE

ALUMINUM STARCH OCTENYLSUCCINATE

ARACHIDYL ALCOHOL

HYDROGENATED PALM GLYCERIDES

DIMETHICONE

BEHENOXY DIMETHICONE

SODIUM STEAROYL GLUTAMATE

HYDROGENATED LECITHIN

RUBUS FRUTICOSUS (BLACKBERRY) LEAF EXTRACT

ARGININE

DIPOTASSIUM GLYCYRRHIZINATE

POLYHYDROXYSTEARIC ACID

BETA-GLUCAN

TOCOPHERYL ACETATE

CAMELLIA SINENSIS LEAF POWDER

ARACHIDYL GLUCOSIDE

MALTODEXTRIN

BEHENYL ALCOHOL

XANTHAN GUM

DISODIUM EDTA

CITRIC ACID

TRIETHOXYCAPRYLYLSILANE

ETHYLHEXYLGLYCERIN

PHENOXYETHANOL

CHLORPHENESIN

STOP USE AND ASK DOCTOR IF RASH OR IRRITATION DEVELOPS AND LASTS.

WARNINGS: FOR EXTERNAL USE ONLY

WHEN USING THIS PRODUCT KEEP OUT OF EYES. RINSE WITH WATER TO REMOVE

KEEP OUT OF REACH OF CHILDREN. CHILDREN UNDER 6 MONTHS OF AGE - ASK A DOCTOR.

IF SWALLOWED, GET MEDICAL HELP OR CONTACT A POISON CENTER RIGHT AWAY.

PURPOSE

HELPS PREVENT SUNBURN

HIGHER SPF GIVES MORE SUNBURN PROTECTION.

DIRECTIONS:

APPLY LIBERALLY TO CLEAN, DRY FACE IN THE MORNING BEFORE SUN EXPOSURE AND AS NEEDED. CHILDREN UNDER 6 MONTHS OF AGE ASK DOCTOR.

PACKAGE LABEL

Enter section text here